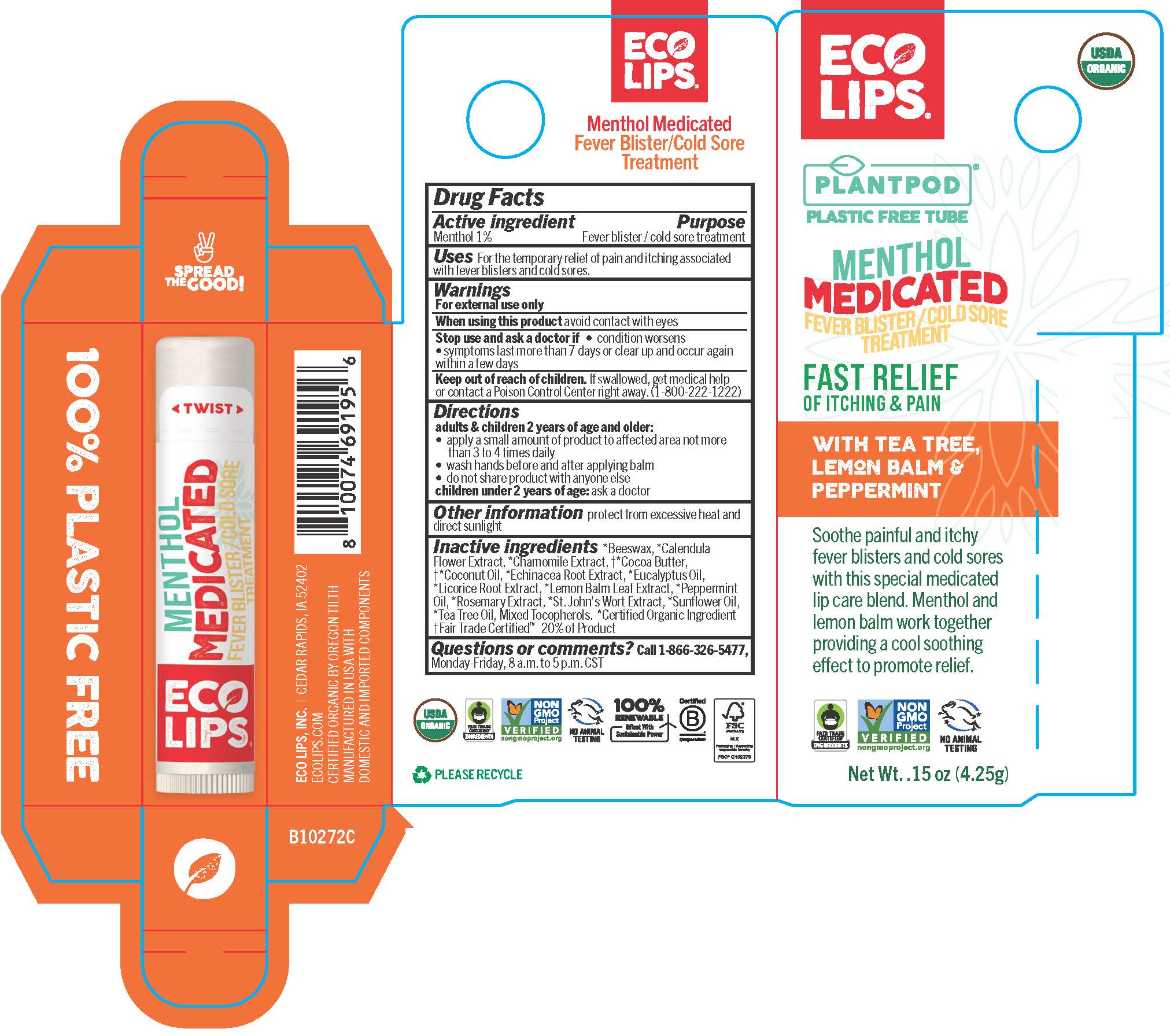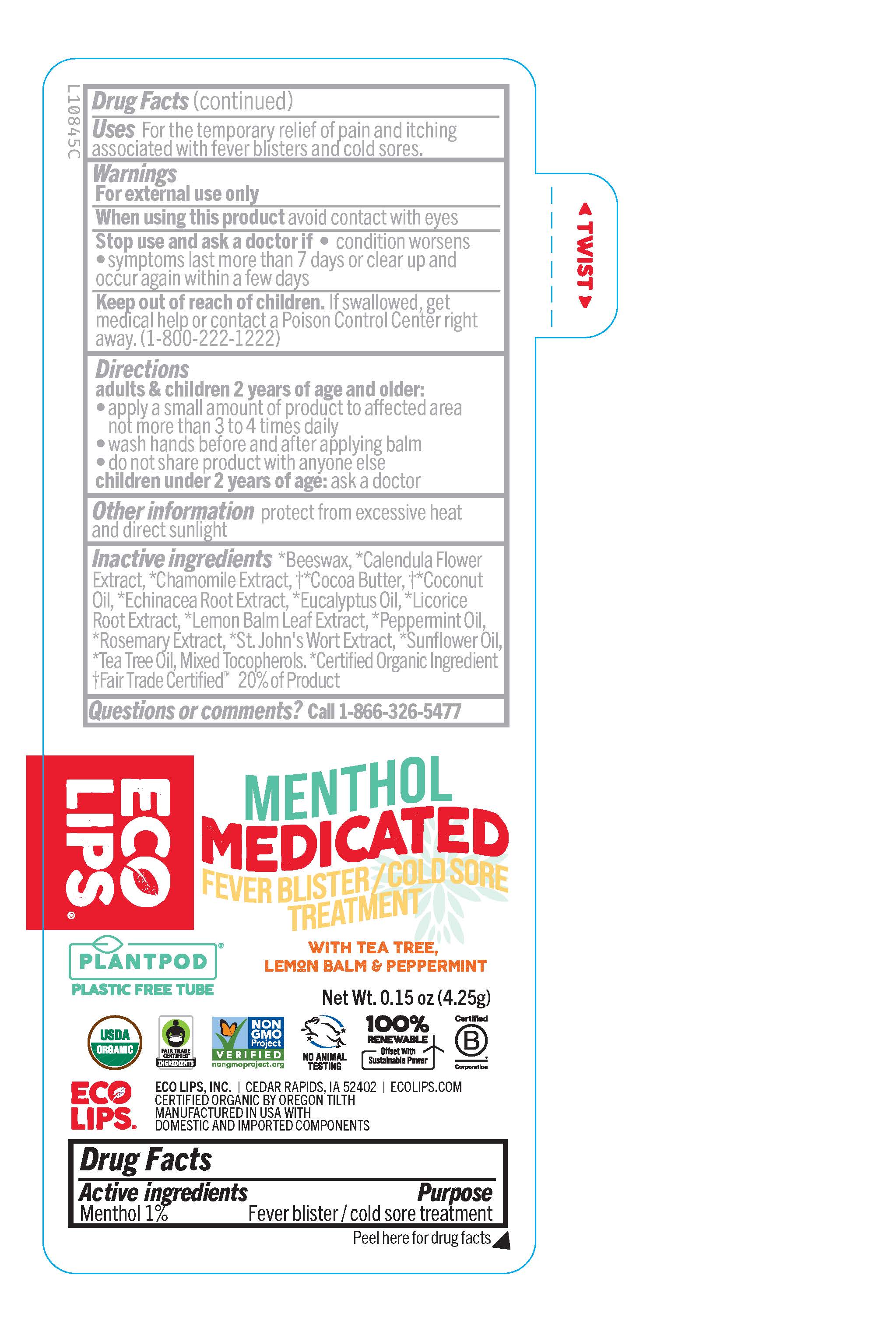 DRUG LABEL: Eco Lips Menthol Medicated Lip Balm
NDC: 75071-010 | Form: STICK
Manufacturer: Eco Lips, Inc.
Category: otc | Type: HUMAN OTC DRUG LABEL
Date: 20250910

ACTIVE INGREDIENTS: MENTHOL 0.0425 g/4.25 g
INACTIVE INGREDIENTS: SUNFLOWER OIL; TEA TREE OIL; CHAMOMILE FLOWER OIL; COCOA BUTTER; ROSEMARY OIL; PEPPERMINT OIL; COCONUT OIL; TOCOPHEROL; CALENDULA OFFICINALIS FLOWER; YELLOW WAX; MELISSA OFFICINALIS LEAF OIL; EUCALYPTUS OIL; ECHINACEA ANGUSTIFOLIA ROOT; ST. JOHN'S WORT; LICORICE

Eco Lips Menthol Medicated Lip Balm

Active Ingredient

Menthol 1%

Purpose

Fever blister / cold sore treatment

INDICATIONS AND USAGE

Uses For the temporary relief of pain and itching associated with fever blisters and cold sores.

Warnings

For external use only

When using this product avoid contact with eyes

Stop use and ask a doctor if

- condition worsens
- symptoms last more than 7 days or clear up and occur again within a few days

Keep out of reach of children. If swallowed, get medical help or contact a Poison Control Center right away. (1-800-222-1222)

Directions

adults & children 2 years of age and older:

- apply a small amount of product to affected area not more than 3 to 4 times daily
- wash hands before and after applying balm
- do not share product with anyone else

children under 2 years of age: ask a doctor

Other information protect from excessive heat and direct sunlight

INACTIVE INGREDIENT

Inactive ingredients *Beeswax, *Calendula Flower Extract, *Chamomile Extract, ⴕ*Cocoa Butter, ⴕ*Coconut Oil, *Echinacea Root Extract, *Eucalyptus Oil, *Licorice Root Extract, *Lemon Balm Leaf Extract, *Peppermint Oil, *Tea Tree Oil, Mixed Tocopherols. *Certified Organic Ingredient ⴕFair Trade Certified™ by Fair Trade USA.® 20% of Product.

Questions or Comments? Call 1-866-326-5477,

Monday-Friday, 8 a.m. to 5 p.m. CST

Carton Text

ECO LIPS

PLANTPOD

PLASTIC FREE TUBE

MENTHOL

MEDICATED

FEVER BLISTER/COLD SORE

TREATMENT

FAST RELIEF

OF ITCHING & PAIN

WITH TEA TREE,

LEMON BALM &

PEPPERMINT

Soothe painful and itchy

fever blisters and cold sores

with this special medicated

lip care blend. Menthol and

lemon balm work together

providing a cool soothing

effect to promote relief.

Net Wt. .15 Oz (4.25 g)

ECO LIPS, INC. | CEDAR RAPIDS, IA 52402

ECOLIPS.COM

CERTIFIED ORGANIC BY OREGON TILTH

MANUFACTURED IN USA WITH

DOMESTIC AND IMPORTED COMPONENTS

100% PLASTIC FREE

SPREAD THE GOOD

RECENT MAJOR CHANGES

The following updates were incorporated into the product labeling beginning 7/2024

Uses For the temporary relief of pain and itching associated with fever blisters and cold sores.

Directions

adults & children 2 years of age and older:

- apply a small amount of product to affected area not more than 3 to 4 times daily
- wash hands before and after applying balm
- do not share product with anyone else

children under 2 years of age: ask a doctor

Label text

ECO LIPS

MENTHOL

MEDICATED

FEVER BLISTER/COLD SORE

TREATMENT

WITH TEA TREEE,

LEMON BALM & PEPPERMINT

PLANTPOD

PLASTIC FREE TUBE

Net Wt. 0.15 oz (4.25g)

ECO LIPS, INC. | CEDAR RAPIDS, IA 52402 | ECOLIPS.COM

CERTIFIED ORGANIC BY OREGON TILTH

MANUFACTURED IN USA WITH

DOMESTIC AND IMPORTED COMPONENTS

Peel here for drug facts